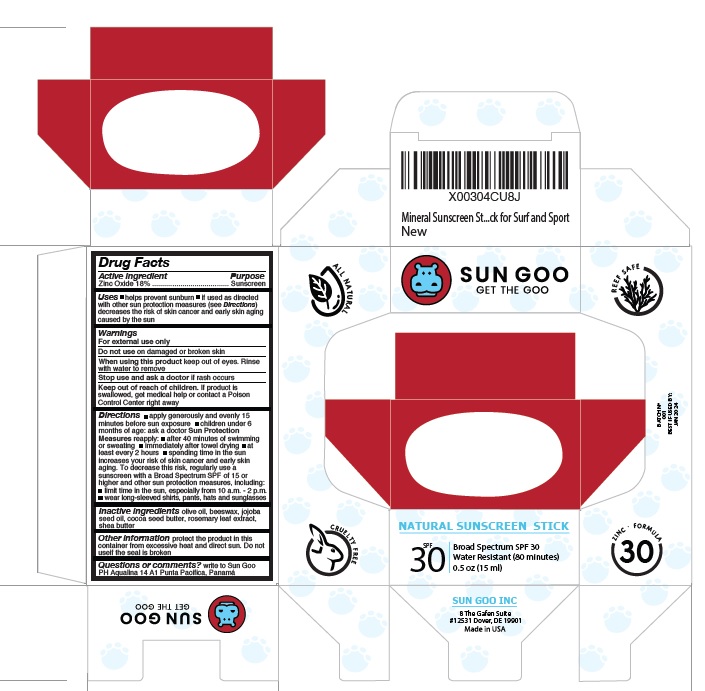 DRUG LABEL: Sun Goo Mineral Sun stick
NDC: 82395-001 | Form: STICK
Manufacturer: Sun Goo Inc
Category: otc | Type: HUMAN OTC DRUG LABEL
Date: 20221130

ACTIVE INGREDIENTS: ZINC OXIDE 18 g/100 mL
INACTIVE INGREDIENTS: OLIVE OIL; YELLOW WAX; JOJOBA OIL; COCOA BUTTER; SHEA BUTTER; ROSEMARY; .ALPHA.-TOCOPHEROL ACETATE

Active Ingredient (s)

Zinc Oxide 18%

Purpose

Sunscreen

Uses

Helps prevent sunburn. If used as directed with other sun protection measures (see Directions) decreases the risk of skin cancer and early skin aging caused by the sun.

Warnings

For external use only
Do not use on damaged or broken skin
When using this product, keep out of eyes. Rinse with water to remove
Stop use and ask doctor if rash occurs
Keep out of reach of children. If a product is swallowed, get medical help or contact a Poison Control Center right away.

Directions

Apply generously and evenly 15 minutes before sun exposure
Children under 6 months of age ask a doctor
Sun protection measures reapply after 40 minutes of swimming or sweating, immediately after towel drying, at least every two hours, spending time in the sun increases your risk of skin cancer and early skin aging. To decrease this risk, regularly use a sunscreen with Broad Spectrum SPF of 15 or higher and other sun protection measures including: limit time in the sun, especially from 10:00 a.m. – 2:00 p.m. wear long-sleeved shirts, pants, hats and sunglasses.

Inactive Ingredients

Olive oil, beeswax, jojoba seed oil, cocoa seed butter, rosemary leaf extract, shea butter

Other information

Protect the product in this container from excessive heat and direct sun. Do not use if the seal is broken